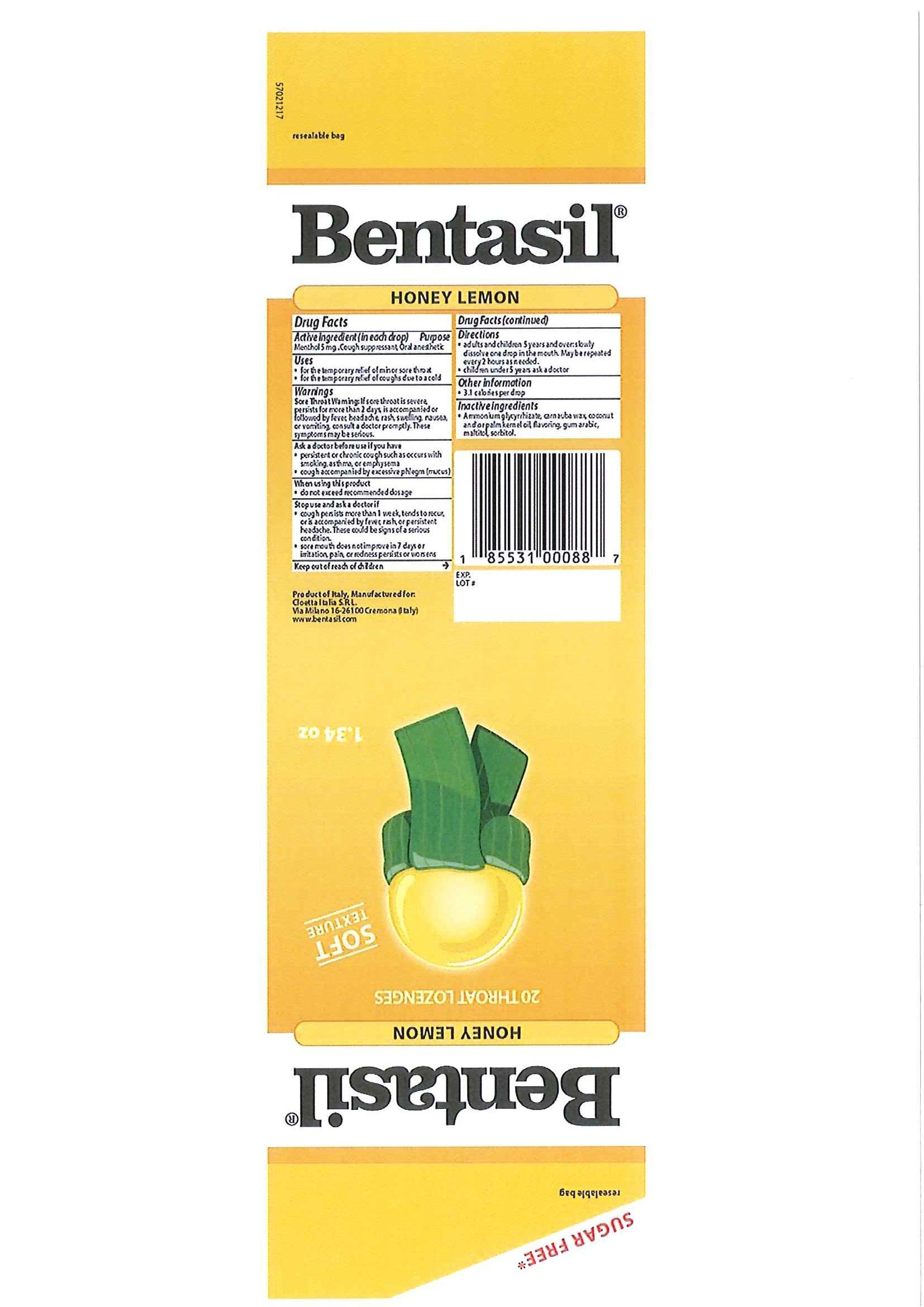 DRUG LABEL: Bentasil
NDC: 63104-004 | Form: LOZENGE
Manufacturer: CLOETTA ITALIA S.r.l.
Category: otc | Type: HUMAN OTC DRUG LABEL
Date: 20140417

ACTIVE INGREDIENTS: MENTHOL 5 mg/1 1
INACTIVE INGREDIENTS: AMMONIUM GLYCYRRHIZATE; CARNAUBA WAX; COCONUT OIL; PALM KERNEL OIL; ACACIA; MALTITOL; SORBITOL

Drug Facts

Active Ingredient

Menthol 5mg

Purpose

Cough Suppressant, Oral Anesthetic

Uses

•for the temporary relief of minor sore throat

•for the temporary relief of coughs due to a cold

Warnings

Sore throat warning: If sore throat is severe, persists for more than 2 days, is accompanied or followed by fever, headache, rash, swelling, nausea, or vomiting, consult a doctor promptly. These symptoms may be serious.

Ask a doctor before use if you have

•persistent or chronic cough such as occurs with smoking, asthma, or emphysema

•cough accompanied by excessive phlegm (mucus)

When using this product

•do not exceed recommended dosage

Stop use and ask a doctor if

•cough persists for more than 1 week, tends to recur, or is accompanied by fever, rash, or persistent headache. These could be signs of a serious condition.

•sore mouth does not improve in 7 days or irritation, pain or redness persists or worsens

Directions

•adults and children 5 years and over: slowly dissolve one drop in the mouth. May be repeated every 2 hours as needed.

•children under 5 years: ask a doctor

Other Information

• 3.1 calories per drop

Inactive Ingredients

•Ammonium glycrrhizate, carnauba wax, coconut and or palm kernel oil, flavoring, gum arabic, maltitol, sorbitol